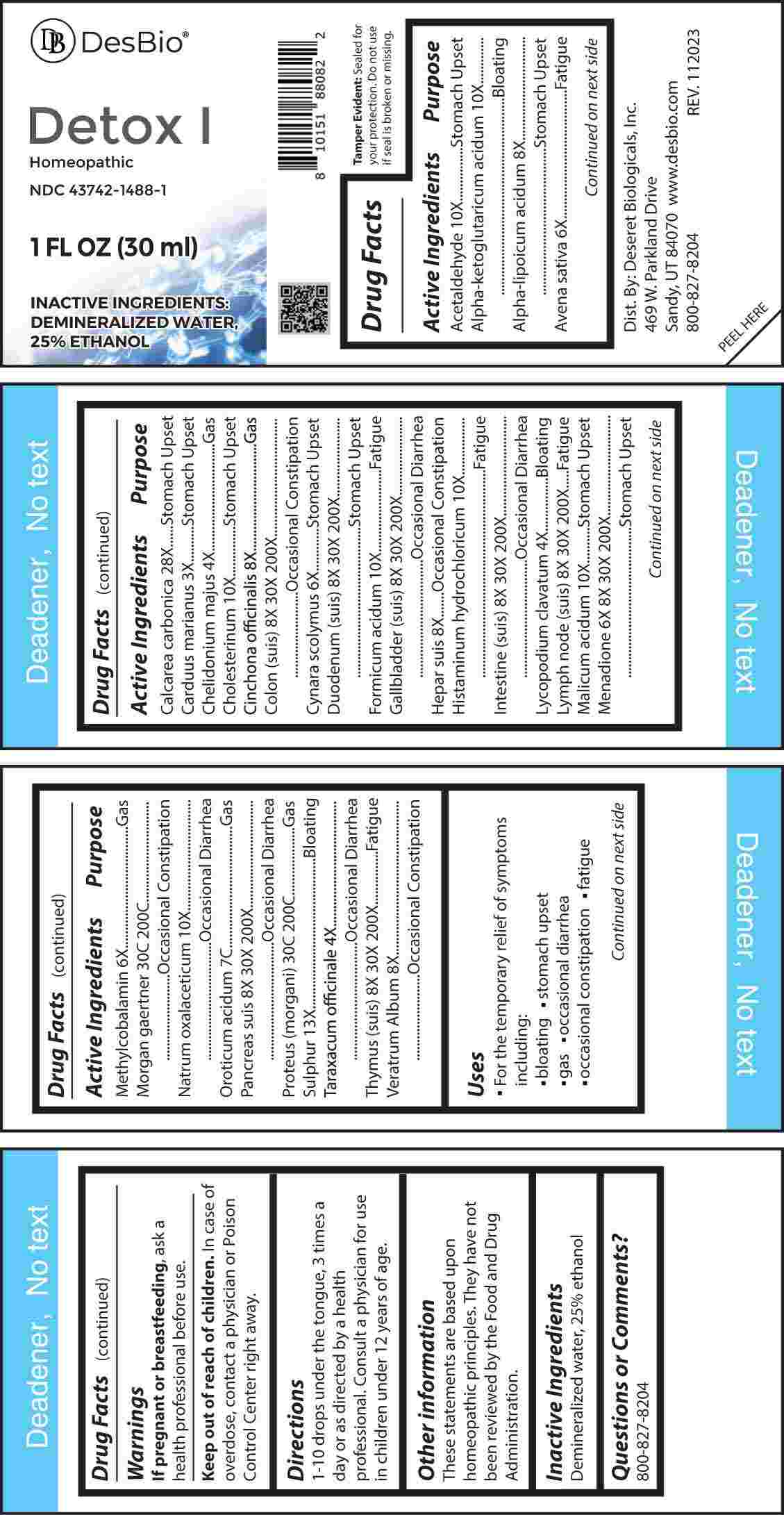 DRUG LABEL: Detox
NDC: 43742-1488 | Form: LIQUID
Manufacturer: Deseret Biologicals, Inc.
Category: homeopathic | Type: HUMAN OTC DRUG LABEL
Date: 20240213

ACTIVE INGREDIENTS: MILK THISTLE 3 [hp_X]/1 mL; CHELIDONIUM MAJUS WHOLE 4 [hp_X]/1 mL; LYCOPODIUM CLAVATUM SPORE 4 [hp_X]/1 mL; TARAXACUM OFFICINALE 4 [hp_X]/1 mL; AVENA SATIVA FLOWERING TOP 6 [hp_X]/1 mL; CYNARA SCOLYMUS LEAF 6 [hp_X]/1 mL; METHYLCOBALAMIN 6 [hp_X]/1 mL; MENADIONE 6 [hp_X]/1 mL; .ALPHA.-LIPOIC ACID 8 [hp_X]/1 mL; CINCHONA OFFICINALIS BARK 8 [hp_X]/1 mL; PORK LIVER 8 [hp_X]/1 mL; VERATRUM ALBUM ROOT 8 [hp_X]/1 mL; SUS SCROFA COLON 8 [hp_X]/1 mL; SUS SCROFA DUODENUM 8 [hp_X]/1 mL; SUS SCROFA GALLBLADDER 8 [hp_X]/1 mL; PORK INTESTINE 8 [hp_X]/1 mL; SUS SCROFA LYMPH 8 [hp_X]/1 mL; SUS SCROFA PANCREAS 8 [hp_X]/1 mL; SUS SCROFA THYMUS 8 [hp_X]/1 mL; ACETALDEHYDE 10 [hp_X]/1 mL; OXOGLURIC ACID 10 [hp_X]/1 mL; CHOLESTEROL 10 [hp_X]/1 mL; FORMIC ACID 10 [hp_X]/1 mL; HISTAMINE DIHYDROCHLORIDE 10 [hp_X]/1 mL; MALIC ACID 10 [hp_X]/1 mL; SODIUM DIETHYL OXALACETATE 10 [hp_X]/1 mL; SULFUR 13 [hp_X]/1 mL; OYSTER SHELL CALCIUM CARBONATE, CRUDE 28 [hp_X]/1 mL; OROTIC ACID MONOHYDRATE 7 [hp_C]/1 mL; SALMONELLA ENTERICA SUBSP. ENTERICA SEROVAR ENTERITIDIS 30 [hp_C]/1 mL; PROTEUS MORGANII 30 [hp_C]/1 mL
INACTIVE INGREDIENTS: WATER; ALCOHOL

DRUG FACTS:

ACTIVE INGREDIENTS:

Acetaldehyde 10X, Alpha-Ketoglutaricum Acidum 10X, Alpha-Lipoicum Acidum 8X, Avena Sativa 6X, Calcarea Carbonica 28X, Carduus Marianus 3X, Chelidonium Majus 4X, Cholesterinum 10X, Cinchona Officinalis 8X, Colon 8X, 30X, 200X, Cynara Scolymus 6X, Duodenum (Suis) 8X, 30X, 200X, Formicum Acidum 10X, Gallbladder (Suis) 8X, 30X, 200X, Hepar Suis 8X, Histaminum Hydrochloricum 10X, Intestine (Suis) 8X, 30X, 200X, Lycopodium Clavatum 4X, Lymph Node (Suis) 8X, 30X, 200X, Malicum Acid 10X, Menadione 6X, 8X, 30X, 200X, Methylcobalamin 6X, Morgan Gaertner 30C, 200C, Natrum Oxalaceticum 10X, Oroticum Acidum 7C, Pancreas (Suis) 8X, 30X, 200X, Proteus (Morgani) 30C, 200C, Sulphur 13X, Taraxacum Officinale 4X, Thymus (Suis) 8X, 30X, 200X, Veratrum Album 8X.

PURPOSE:

Acetaldehyde – Stomach Upset, Alpha-Ketoglutaricum Acidum - Bloating, Alpha-Lipoicum Acidum – Stomach Upset, Avena Sativa - Fatigue, Calcarea Carbonica – Stomach Upset, Carduus Marianus – Stomach Upset, Chelidonium Majus - Gas, Cholesterinum – Stomach Upset, Cinchona Officinalis - Gas, Colon (Suis) – Occasional Constipation, Cynara Scolymus – Stomach Upset, Duodenum (Suis) – Stomach Upset, Formicum Acidum - Fatigue, Gallbladder (Suis) – Occasional Diarrhea, Hepar Suis – Occasional Constipation, Histaminum Hydrochloricum - Fatigue, Intestine (Suis) – Occasional Diarrhea, Lycopodium Clavatum - Bloating, Lymph Node (Suis) - Fatigue, Malicum Acid – Stomach Upset, Menadione – Stomach Upset, Methylcobalamin - Gas, Morgan Gaertner – Occasional Constipation, Natrum Oxalaceticum – Occasional Diarrhea, Oroticum Acidum - Gas, Pancreas Suis– Occasional Diarrhea, Proteus (Morgani) - Gas, Sulphur - Bloating, Taraxacum Officinale – Occasional Diarrhea, Thymus (Suis) - Fatigue, Veratrum Album – Occasional Constipation.

USES:

• For the temporary relief of symptoms including:

• bloating • stomach upset

• gas • occasional diarrhea

• occasional constipation • fatigue

These statements are based upon homeopathic principles. They have not been reviewed by the Food and Drug Administration.

WARNINGS:

If pregnant or breast-feeding, ask a health professional before use.

Keep out of reach of children. In case of overdose, contact a physician or Poison Control Center right away.

Tamper Evident: Sealed for your protection. Do not use if seal is broken or missing.

KEEP OUT OF REACH OF CHILDREN:

In case of overdose, contact a physician or Poison Control Center right away.

DIRECTIONS:

1-10 drops under the tongue, 3 times a day or as directed by a health professional. Consult a physician for use in children under 12 years of age.

INACTIVE INGREDIENTS:

Demineralized water, 25% ethanol

QUESTIONS:

Dist. By: Deseret Biologicals, Inc.

469 W. Parkland Drive

Sandy, UT 84070 www.desbio.com

800-827-8204

PACKAGE LABEL DISPLAY:

Des Bio

Detox I

Homeopathic

NDC 43742-1488-1

1 FL OZ (30 ml)